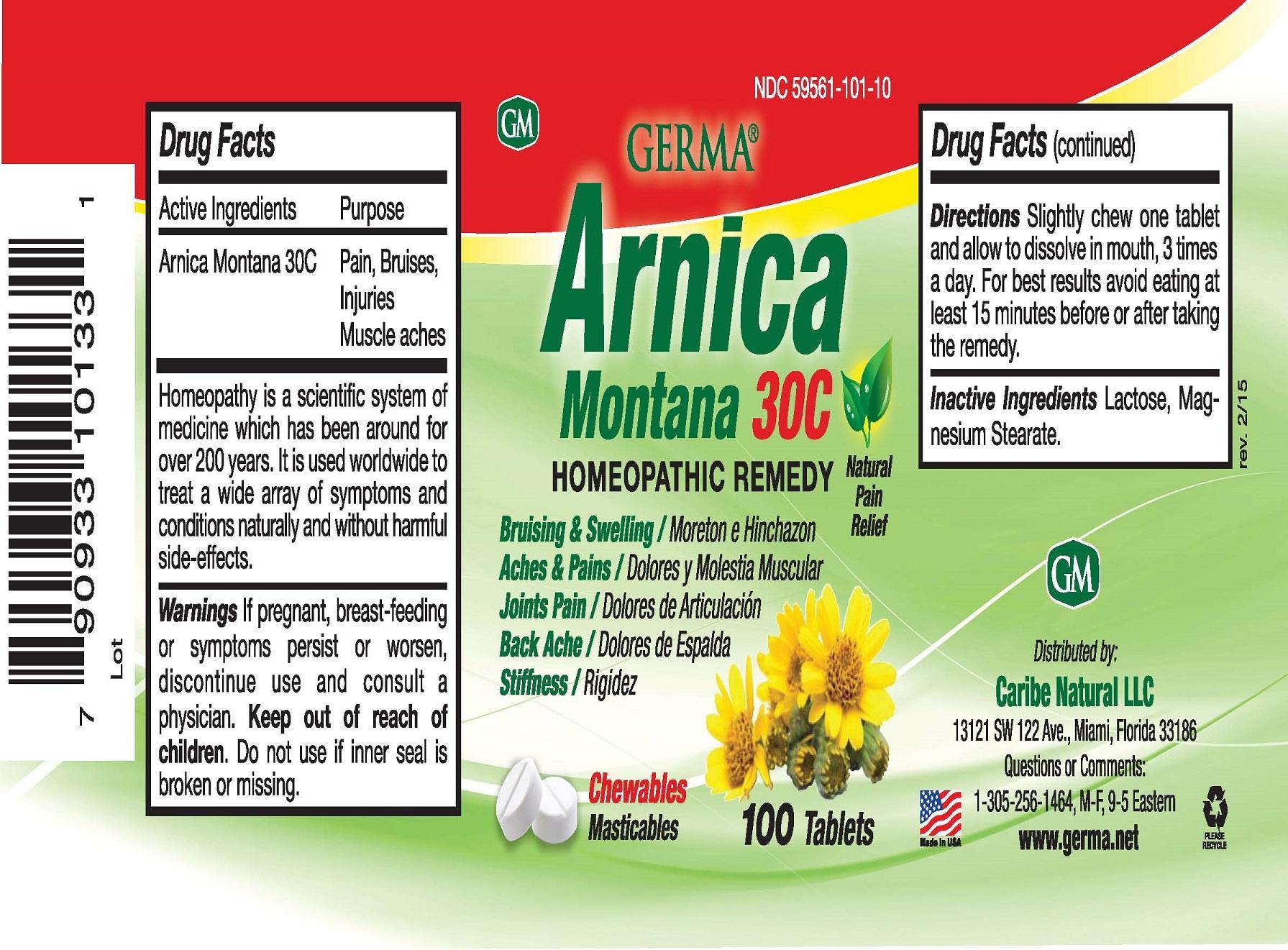 DRUG LABEL: Germa Arnica Montana 30C
NDC: 59561-101 | Form: TABLET
Manufacturer: Caribe Natural, Inc.
Category: homeopathic | Type: HUMAN OTC DRUG LABEL
Date: 20150409

ACTIVE INGREDIENTS: ARNICA MONTANA 30 [hp_C]/1 1
INACTIVE INGREDIENTS: LACTOSE; MAGNESIUM STEARATE

Active Ingredients Purpose

Arnica Montana 30C Pain, Bruises, Injuries Muscle Aches

PURPOSE

Bruising & Swelling / Moreton e Hinchazon

Aches & Pains / Dolores y Molestia Musuclar

Joints Pain / Dolores de Articulacion

Back Ache / Dolores de Espalda

Stiffness / Rigidez

Keep out of reach of children.

INDICATIONS AND USAGE

Homeopathy is a scientific system of medicine which has been around for over 200 years. It is used worldwide to treat a wide array of symptoms and conditions naturally and without harmful side-effects.

Directions

Slighly chew one table and allow to dissolve in mouth, 3 times a day. For best results avoid eating at least 15 minutes before or after taking the remedy.

Warnings

If pregnant, breastfeeding or symptoms persist or worsen, discontinue use and consult a physician. Do not use if inner seal is broken or missing.

Inactive Ingredients

Lactose, magnesium stearate